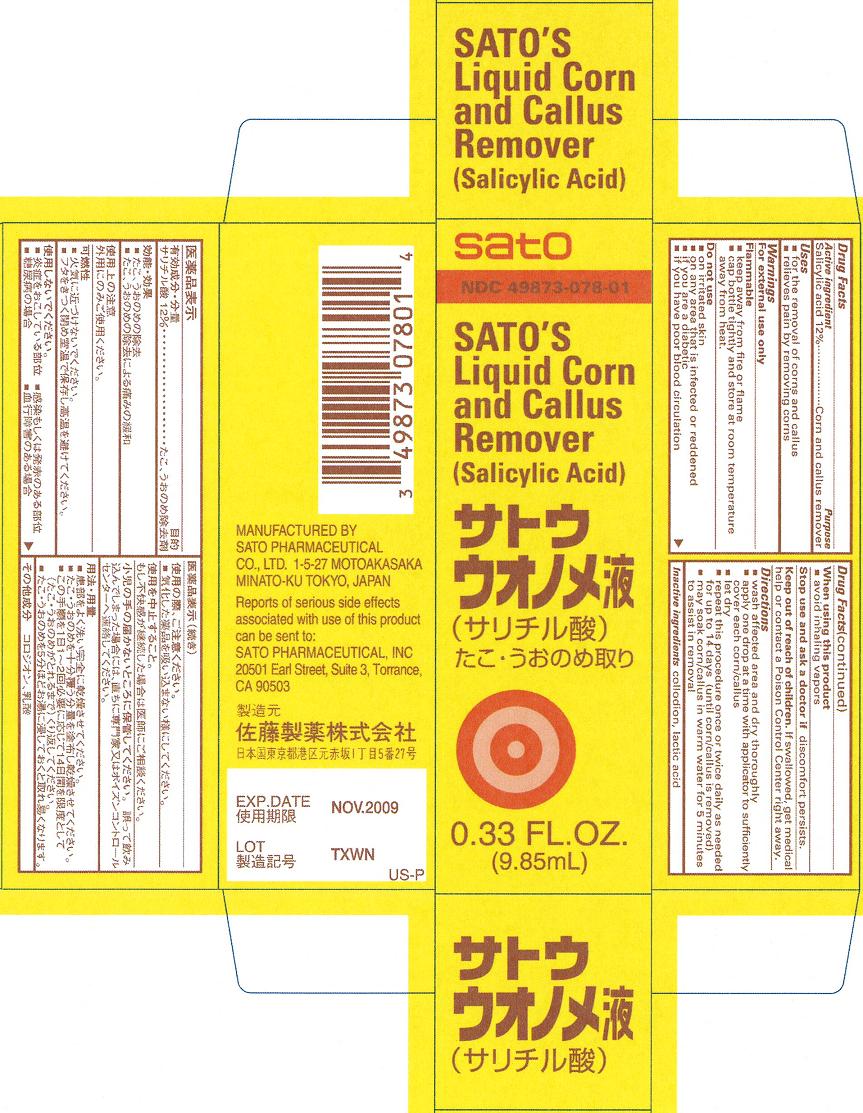 DRUG LABEL: Satos Corn and Callus Remover
NDC: 49873-078 | Form: LIQUID
Manufacturer: Sato Pharmaceutical Co., Ltd.
Category: otc | Type: HUMAN OTC DRUG LABEL
Date: 20231204

ACTIVE INGREDIENTS: SALICYLIC ACID 12 g/100 mL
INACTIVE INGREDIENTS: PYROXYLIN; LACTIC ACID

Satos Corn and Callus Remover

Active ingredient

Salicylic acid 12%

Purpose

Salicylic acid...Corn and callus remover

Uses
■ for the removal of corns and callus
■ relieves pain by removing corns

WARNINGS

OTHER SAFETY INFORMATION

For external use only

ENVIRONMENTAL WARNING

Flammable
■ keep away from fire or flame
■ cap bottle tightly and store at room temperature away from heat.

Do not use
■ on irritated skin
■ on any area that is infected or reddened
■ if you are a diabetic
■ if you have poor blood circulation

When using this product
■ avoid inhaling vapors

Stop use and ask a doctor if discomfort persists.

Keep out of reach of children. If swallowed, get medical help or contact a Poison Control Center right away.

Directions
■ wash affected area and dry thoroughly
■ apply one drop at a time with applicator to sufficiently cover each corn/callus
■ let dry
■ repeat this procedure once or twice daily as needed for up to 14 days (until corn/callus is removed)
■ may soak corn/callus in warm water for 5 minutes to assist in removal

Inactive ingredients collodion, lactic acid

PACKAGE LABEL

satoliqcorncart.jpg